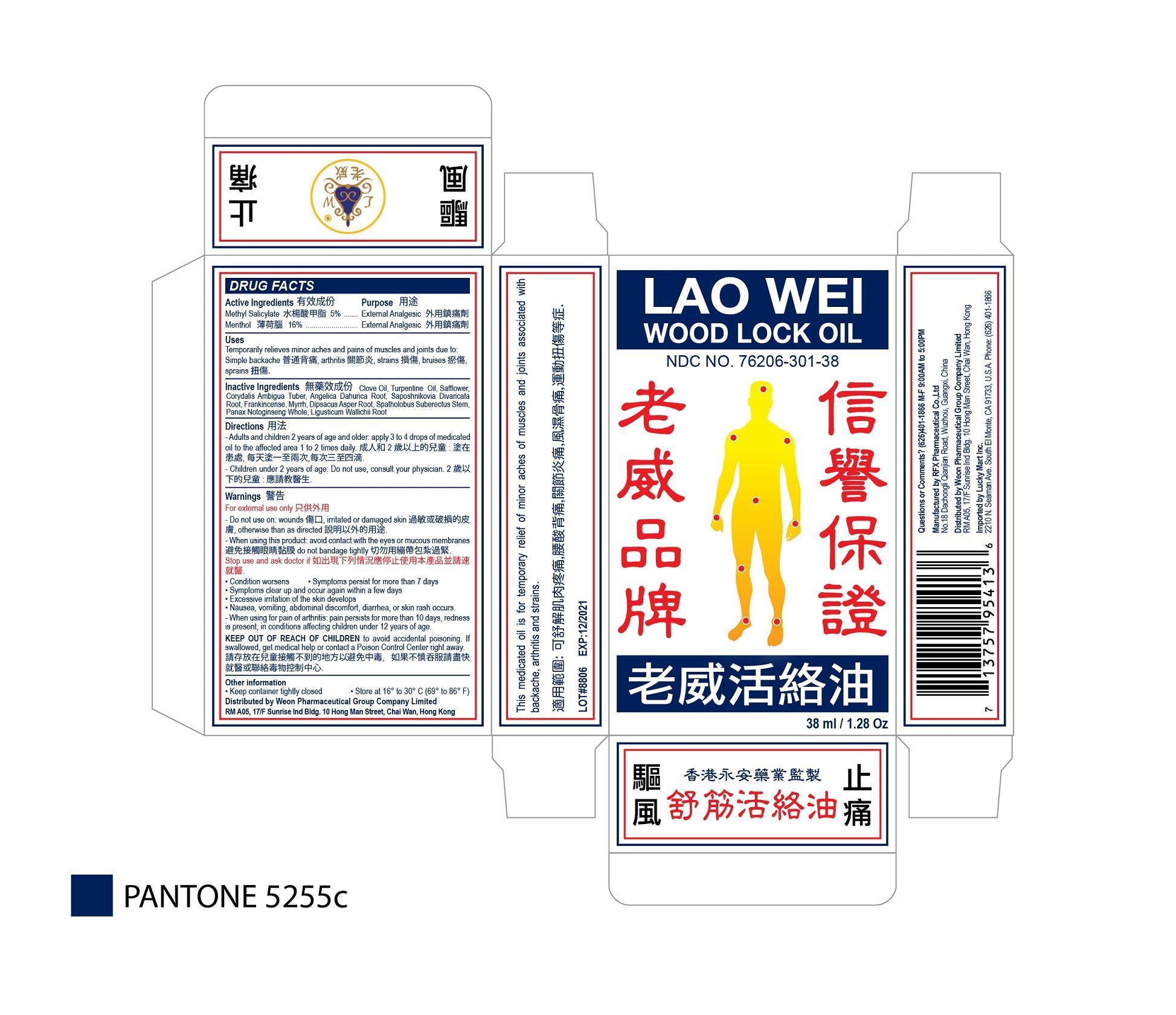 DRUG LABEL: Lao Wei Wood Lock Oil
NDC: 76206-301 | Form: OIL
Manufacturer: RFX Pharmaceutical Co Ltd
Category: otc | Type: HUMAN OTC DRUG LABEL
Date: 20150820

ACTIVE INGREDIENTS: METHYL SALICYLATE 5 g/100 mL; MENTHOL 16 g/100 mL
INACTIVE INGREDIENTS: CLOVE OIL; TURPENTINE OIL; SAFFLOWER; CORYDALIS AMBIGUA TUBER; ANGELICA DAHURICA ROOT; SAPOSHNIKOVIA DIVARICATA ROOT; FRANKINCENSE; MYRRH; DIPSACUS ASPER ROOT; SPATHOLOBUS SUBERECTUS STEM; PANAX NOTOGINSENG WHOLE; LIGUSTICUM WALLICHII ROOT

RFX Pharmaceutical Co Ltd

Active Ingredients

Methyl Salicylate 5%

Menthol 16%

Purpose

Methyl Salicylate External Analgesic

Menthol External Analgesic

Uses

Temporarily relieves minor aches and pains of muscles and joints due to: simple backaches, arthritis, strains, bruises and sprains.

Directions

Adults and children 2 years of age and older: apply 3 to 4 drops of medicated oil to the affected area 1 to 2 times daily. Children under 2 years of age: Do not use, consult your physician.

Warnings

For external use only. Do not use on wounds, irritated or damaged skin, otherwise than as directed. When using this product, avoid contact with the eyes or mucous membranes. Do not bandage tightly.

Keep out of reach of children to avoid accidental poinsoning. If swallowed, get medical help or contact a Poison Center right away.

Stop use and ask a doctor if

Condition worsens

Symptoms persist for more than 7 days

Symptoms clear up and occur again within a few days

Excessive irritation of the skin develops

Nausea, vomitting, abdominal discomfort, diarrhea, or skin rash occurs

When using for pain of arthritis: pain persits for more than 10 days, redness is present, in conditions affecting children 12 years of age.

Other Information

Keep container tightly closed. Store at 16 to 30°C (69 to 86°F).

Inactive Ingredients

CLOVE OIL, TURPENTINE OIL, SAFFLOWER, CORYDALIS AMBIGUA TUBER, ANGELICA DAHURICA ROOT, SAPOSHNIKOVIA DIVARICATA ROOT, FRANKINCENSE, MYRRH, DIPSACUS ASPER ROOT, SPATHOLOBUS SUBERECTUS STEM, PANAX NOTOGINSENG WHOLE, LIGUSTICUM WALLICHII ROOT

Questions or Comments? (626)401-1866, M-F 9:00 am to 5:00 pm

Manufactured by RFX Pharmaceutical Co.; Ltd
No. 18, Dachongli Qianjian Road, Wuzhou, Guangxi, China

Distributed by WEON PHARMACEUTICAL GROUP COMPANY LIMITED. RM A05，17/F SUNRISE IND BLDG, 10 HONG MAN ST CHAI WAN, HONG KONG

Imported by Lucky Mart Inc.
2210 N. Seaman Ave, South El Monte, CA 91733, U.S.A
Phone: (626)401-1866